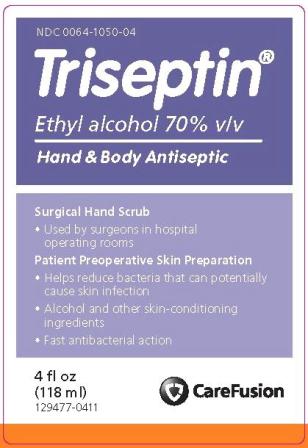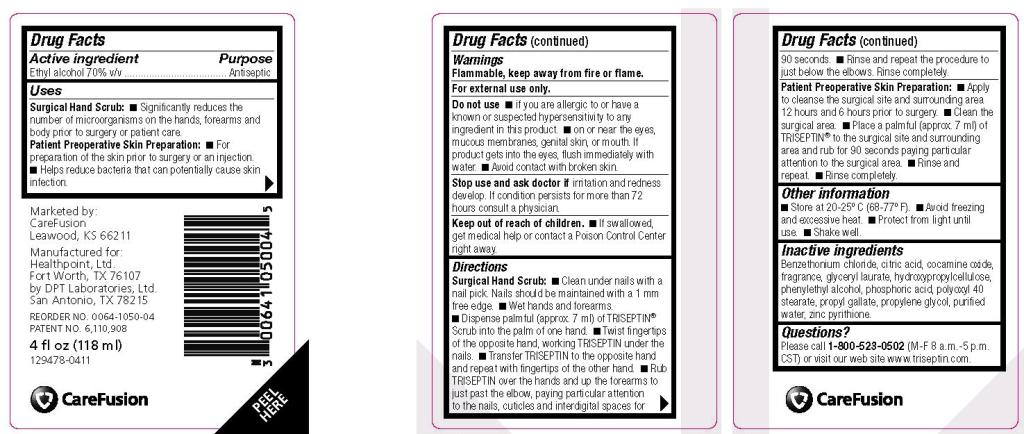 DRUG LABEL: TRISEPTIN
NDC: 0064-1050 | Form: LOTION
Manufacturer: HEALTHPOINT, LTD
Category: otc | Type: HUMAN OTC DRUG LABEL
Date: 20120104

ACTIVE INGREDIENTS: ALCOHOL .7 mL/1 mL
INACTIVE INGREDIENTS: BENZETHONIUM CHLORIDE; CITRIC ACID MONOHYDRATE; COCAMINE OXIDE; GLYCERYL LAURATE; HYDROXYPROPYL CELLULOSE; PHENYLETHYL ALCOHOL; PHOSPHORIC ACID; POLYOXYL 40 STEARATE; PROPYL GALLATE; PROPYLENE GLYCOL; WATER; PYRITHIONE ZINC

TRISEPTIN Hand and Body Antiseptic – alcohol lotion
CareFusion

Drug Facts

Active ingredient

Ethyl alcohol 70% v/v

PURPOSE

Antiseptic

Uses

Surgical Hand Scrub:

- Significantly reduces the number of microorganisms on the hands, forearms and body prior to surgery or patient care.

Patient Preoperative Skin Preparation:

- For preparation of the skin prior to surgery or an injection.
- Helps reduce bacteria that can potentially cause skin infection.

Warnings

- Flammable, keep away from fire or flame.
- For external use only.
- Do not use
- if you are allergic to or have a known or suspected hypersensitivity to any ingredient in this product.
- on or near the eyes, mucous membranes, genital skin, or mouth. If product gets into the eyes, flush immediately with water.
- Avoid contact with broken skin.
- Stop use and ask doctor if irritation and redness develop. If condition persists for more than 72 hours consult a physician.

- Keep out of reach of children.

- If swallowed, get medical help or contact a Poison Control Center right away.

Directions

Surgical Hand Scrub:

- Clean under nails with a nail pick. Nails should be maintained with a 1 mm free edge.
- Wet hands and forearms.
- Dispense palmful (approx. 7 ml) of TRISEPTIN Scrub into the palm of one hand.
- Twist fingertips of the opposite hand, working TRISEPTIN under the nails.
- Transfer TRISEPTIN to the opposite hand and repeat with fingertips of the other hand.
- Rub TRISEPTIN over the hands and up the forearms to just past the elbow, paying particular attention to the nails, cuticles and interdigital spaces for 90 seconds.
- Rinse and repeat the procedure to just below the elbows. Rinse completely.

Patient Preoperative Skin Preparation:

- Apply to cleanse the surgical site and surrounding area 12 hours and 6 hours prior to surgery.
- Clean the surgical area.
- Place a palmful (approx. 7 ml) of TRISEPTIN to the surgical site and surrounding area and rub for 90 seconds paying particular attention to the surgical area.
- Rinse and repeat.
- Rinse completely.

Other information

- Store at 20-25º C (68-77º F).
- Avoid freezing and excessive heat.
- Protect from light until use.
- Shake well.

Inactive ingredients

Benzethonium chloride, citric acid, cocamine oxide, fragrance, glyceryl laurate, hydroxypropylcellulose, phenylethyl alcohol, phosphoric acid, polyoxyl 40 stearate, propyl gallate, propylene glycol, purified water, zinc pyrithione.

Questions?

Please call 1-800-523-0502 (M-F 8 a.m.-5 p.m. CST) or visit our web site www.triseptin.com.

Marketed by:
CareFusion
Leawood, KS 66211

Manufactured for:
Healthpoint, Ltd.
Fort Worth, TX 76107
by DPT Laboratories, Ltd.
San Antonio, Texas 78215

REORDER NO. 0064-1050-04
PATENT NO. 6,110,908

4 fl oz (118 ml)
129478-0411

PRINCIPAL DISPLAY PANEL

NDC 0064-1050-04

Triseptin®
Ethyl alcohol 70% v/v
Hand & Body Antiseptic

Surgical Hand Scrub

- Used by surgeons in hospital operating rooms

Patient Preoperative Skin Preparation

- Helps reduce bacteria that can potentially cause skin infection
- Alcohol and other skin-conditioning ingredients
- Fast antibacterial action

4 fl oz
(118 ml)
129477-0411

CareFusion